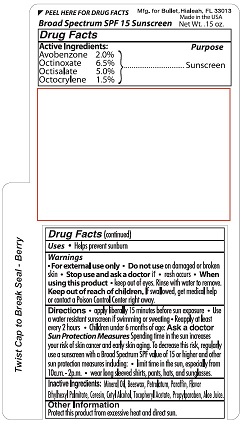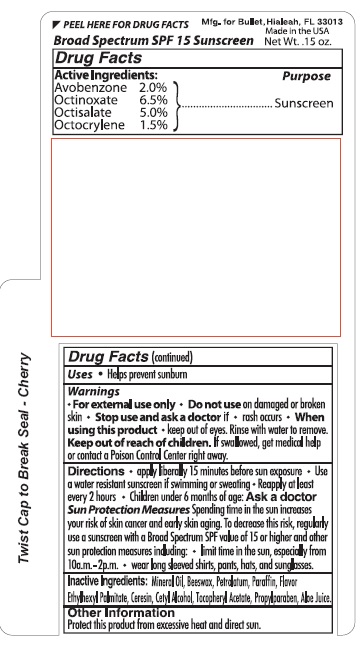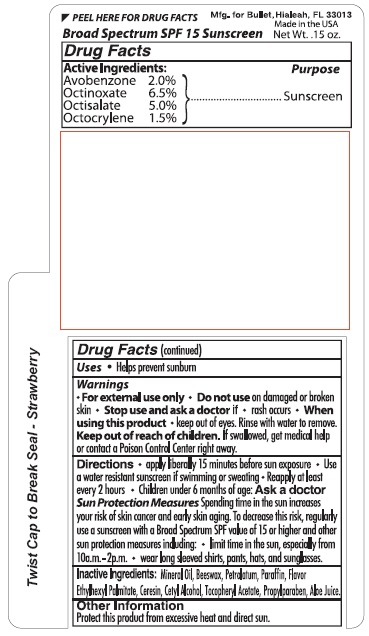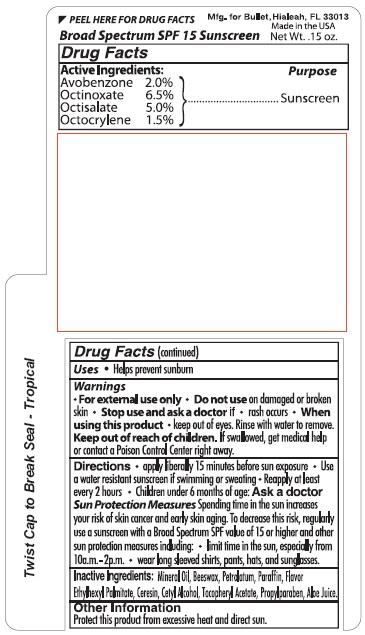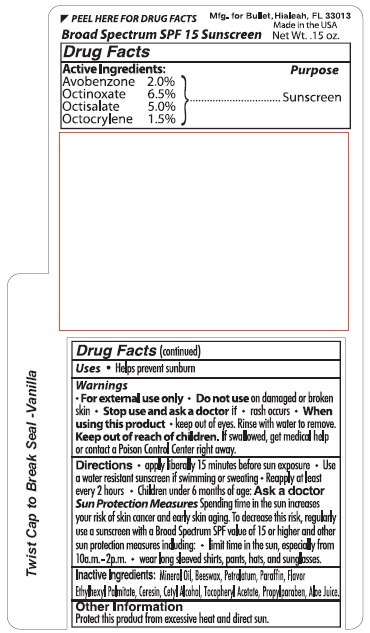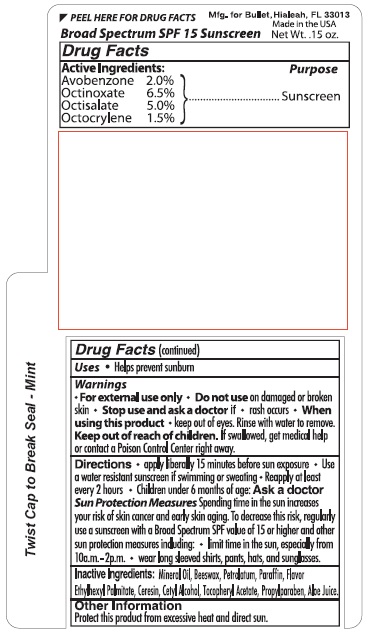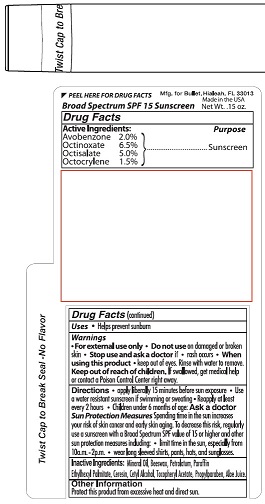 DRUG LABEL: Bullet Line
NDC: 65692-1006 | Form: STICK
Manufacturer: Raining Rose, Inc
Category: otc | Type: HUMAN OTC DRUG LABEL
Date: 20231104

ACTIVE INGREDIENTS: AVOBENZONE 2.0 mg/1 g; OCTINOXATE 6.5 mg/1 g; OCTISALATE 5.0 mg/1 g; OCTOCRYLENE 1.5 mg/1 g
INACTIVE INGREDIENTS: MINERAL OIL; WHITE WAX; YELLOW WAX; PETROLATUM; PARAFFIN; ETHYLHEXYL PALMITATE; CERESIN; CETYL ALCOHOL; ALPHA-TOCOPHEROL ACETATE; PROPYLPARABEN; ALOE VERA LEAF

Bullet Line

Drug Facts

Active ingredient

Purpose

Uses

Warnings:
• For external use only • Do not use on damaged or broken
skin. • Stop use and ask a doctor if • rash occurs • When
using this product • keep out of eyes. Rinse with water to remove.

Keep out of reach of children. If swallowed get medical help
or contact a Poison Control Center right away.

Directions
• Apply liberally 15 minutes before sun exposure • Use
a water-resistant sunscreen if swimming or sweating • Reapply at least
every 2 hours • Children under 6 months of age: Ask a doctor

OTHER SAFETY INFORMATION

Sun Protection Measures Spending time in the sun increases your
risk of skin cancer and early skin aging. To decrease this risk, regularly
use a sunscreen with a Broad-Spectrum SPF value of 15 or higher and
other protection measures including: • limit time in the sun, especially from
10a.m. - 2p.m. • wear long sleeved shirts, pants, hat, and sunglasses.

Inactive ingredients: Mineral oil, Beeswax, Petrolatum, Paraffin

Ethylhexyl Palmitate, Ceresin, Cetyl Alcohol, Tocopheryl Acetate, Propylparaben, Aloe Juice.

Other Information
Protect this product from excessive heat and direct sun.

Package Labeling

Twist Cap to Break Seal

Broad Spectrum SPF 15 Sunscreen

Mfg. for Bullet, Hialeah, FL 33013

Made in the USA

Net Wt. .15 oz.

No-flavor

Berry

Cherry

Mint

Strawberry

Tropical

Vanilla

res